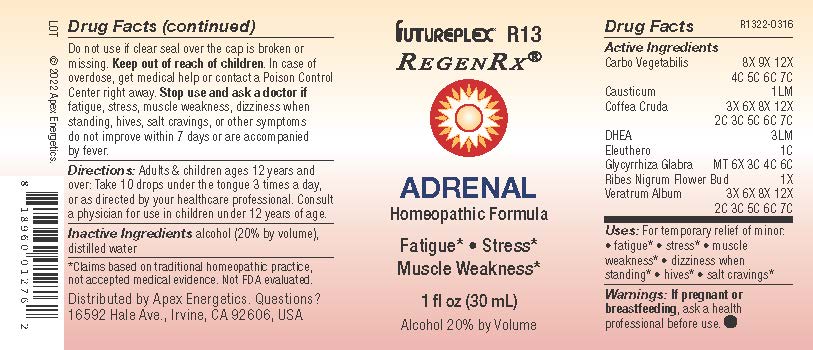 DRUG LABEL: R13
NDC: 63479-1813 | Form: SOLUTION
Manufacturer: Apex Energetics Inc.
Category: homeopathic | Type: HUMAN OTC DRUG LABEL
Date: 20250108

ACTIVE INGREDIENTS: ACTIVATED CHARCOAL 7 [hp_C]/1 mL; CAUSTICUM 1 [hp_Q]/1 mL; ARABICA COFFEE BEAN 7 [hp_C]/1 mL; PRASTERONE 3 [hp_Q]/1 mL; GLYCYRRHIZA GLABRA 6 [hp_C]/1 mL; RIBES NIGRUM FLOWER BUD 1 [hp_X]/1 mL; ELEUTHERO 1 [hp_C]/1 mL; VERATRUM ALBUM ROOT 7 [hp_C]/1 mL
INACTIVE INGREDIENTS: ALCOHOL; WATER

R13

Active Ingredients
Carbo Vegetabilis | 8X 9X 12X 4C 5C 6C 7C
Causticum | 1LM
Coffea Cruda | 3X 6X 8X 12X 2C 3C 5C 6C 7C
DHEA | 3LM
Eleuthero | 1C
Glycyrrhiza Glabra | MT 6X 3C 4C 6C
Ribes Nigrum Flower Bud | 1X
Veratrum Album | 3X 6X 8X 12X 2C 3C 5C 6C 7C

INDICATIONS AND USAGE

Uses:

For temporary relief of minor:

fatigue*

stress*

muscle weakness*

dizziness when standing*

hives*

salt cravings*

*Claims based on traditional homeopathic practice, not accepted medical evidence. Not FDA evaluated.

Warnings:

PREGNANCY OR BREAST FEEDING

If pregnant or breastfeeding, ask a health professional before use.

Do not use if clear seal over the cap is broken or missing.

Keep out of reach of children. In case of overdose, get medical help or contact a Poison Control Center right away.

Stop use and ask a doctor if fatigue, stress, muscle weakness, dizziness when standing, hives, salt cravings, or other symptoms
do not improve within 7 days or are accompanied by fever.

Directions:

Adults & children ages 12 years and over: Take 10 drops under the tongue 3 times a day, or as directed by your healthcare professional. Consult a physician for use in children under 12 years of age.

Inactive Ingredients

alcohol (20% by volume), distilled water

Distributed by Apex Energetics. Questions?
16592 Hale Ave., Irvine, CA 92606, USA

PACKAGE LABEL

FUTUREPLEX® R13

REGENRX®

ADRENAL
Homeopathic Formula

Fatigue • Stress

Muscle Weakness

1 fl oz (30 mL)

Alcohol 20% by Volume